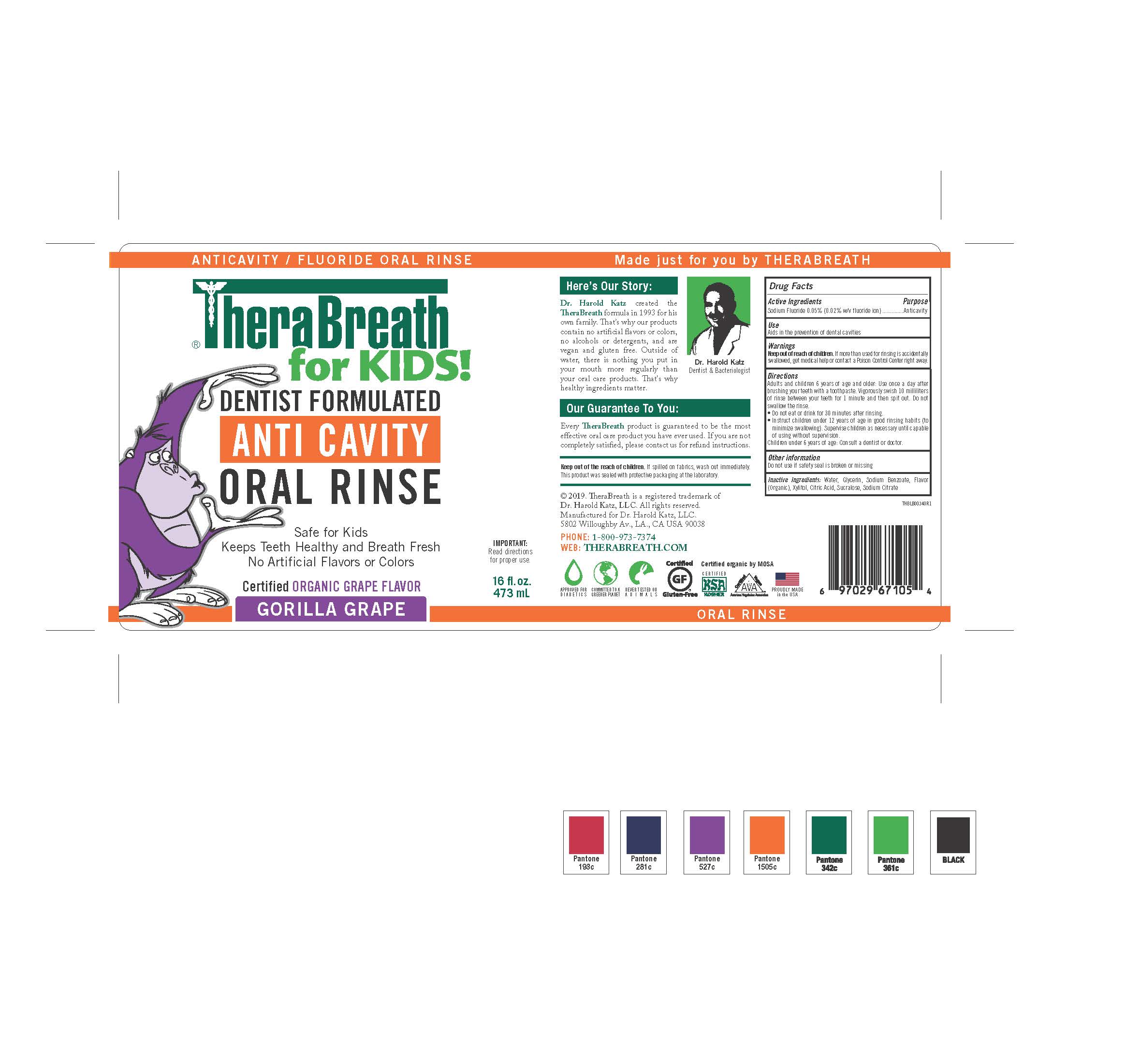 DRUG LABEL: TheraBreath for Kids Anti Cavity Oral Rinse
NDC: 72551-254 | Form: RINSE
Manufacturer: Dr. Harold Katz, LLC
Category: otc | Type: HUMAN OTC DRUG LABEL
Date: 20220203

ACTIVE INGREDIENTS: SODIUM FLUORIDE 0.0005 g/1 g
INACTIVE INGREDIENTS: WATER; XYLITOL; ANHYDROUS CITRIC ACID; SODIUM BENZOATE; GLYCERIN; GRAPE; SODIUM CITRATE; SUCRALOSE

TheraBreath for Kids Anti Cavity Oral Rinse

Active Ingredient

Sodium Fluoride 0.05% (0.02%) w/v fluoride ion)

Purpose

Anticavity

Use

Aids in the prevention of dental cavities

Warnings

Keep Out Of Reach of Children.

Warnings

If more than used for rinsing is accidentally swallowed, get help or contact a Poison Control Center right away.

Directions

• Adults and children 6 years of age and older: Use once a day after brushing your teeth with a
toothpaste. Vigorously swish 10 milliliters of rinse between your teeth for 1 minute and then spit out. Do not

swallow the rinse.
• Do not eat or drink for 30 minutes after rinsing.
• Instruct children under 12 years of age in good rinsing habits (to minimize swallowing).
Supervise children as necessary until capable of using without supervision.
• Children under 6 years of age: Consult a dentist or doctor.

Other information

Do not use if safety seal is broken or missing

Inactive Ingredients

Water, Glycerin, Sodium Benzoate, Flavor (Organic), Xylitol, Citric Acid, Sucralose, Sodium Citrate